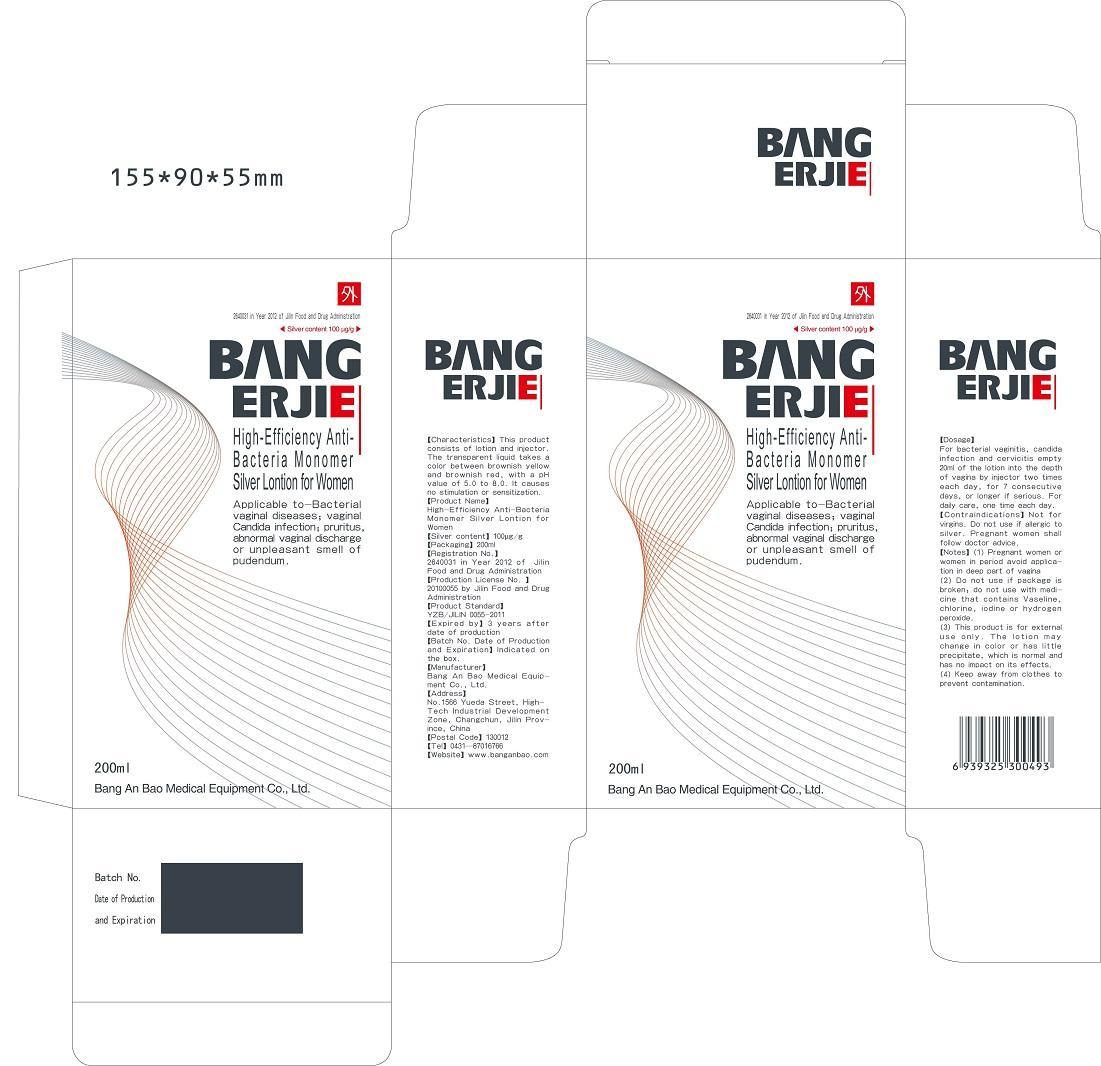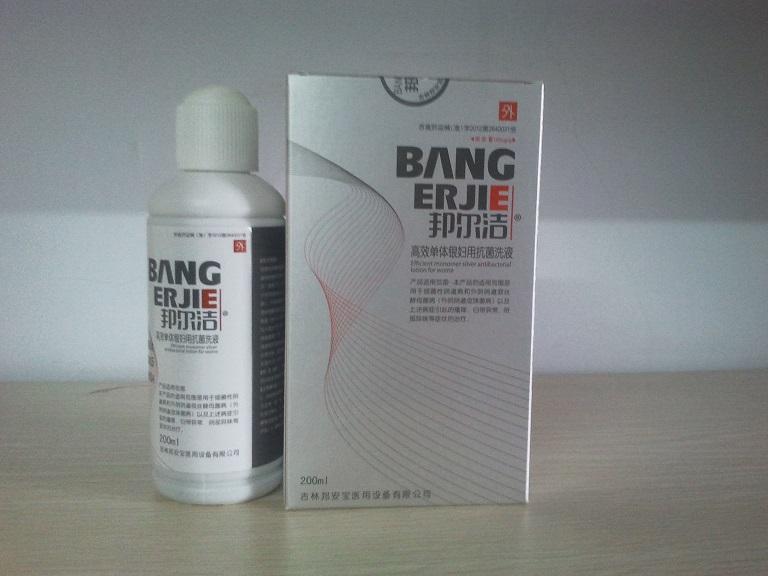 DRUG LABEL: Bang Er Jie High-Efficiency Anti-Bacteria Monomer Silver -Lotion for Women
NDC: 60659-0102 | Form: LOTION
Manufacturer: Bang An Bao Medical Equipment Co., Ltd.
Category: homeopathic | Type: HUMAN OTC DRUG LABEL
Date: 20130921

ACTIVE INGREDIENTS: Silver 20 mg/200 mL
INACTIVE INGREDIENTS: Water 199980 mg/200 mL

Active ingredient

Silver content: 100 μg/g

Purpose

Anti-Bacteria

Monomer silver gel is a highly active agent which significantly suppresses and eliminates Candida albicans, Escherichia coli, Staphylococcus aureus and Pseudomonas aeruginosa within and around the vagina, prevents and cures inflammation, accelerates the recovery of wounds and lesioned tissues regardless of vagina pH without affecting normal vaginal bacteria.

Indcations and usage

Indication to bacterial vaginal diseases; vaginal candida infection; cervicitis; pruritus; abnormal vaginal discharge, or unpleasant smell due to vaginitis.

Topical use: Apply on the affected area of vagina.

Dosage

For bacterial vaginitis, candida infection and cervicitis empty 20ml of the lotion into the depth of vagina by injector two times each day, for 7 consecutive days, or longer if serious. For daily care, one time each day.

Warnings

Contraindications:
1, For external use only.

2, Not for virgins.

3, Do not use if allergic to silver.

4, Pregnant women shall follow doctor advice.

Notes:
1, Pregnant women or women in period avoid application in deep part of vagina
2, Do not use if package is broken; do not use with medicine that contains Vaseline, chlorine, iodine or hydrogen peroxide.
3, This product is for external use only; do not take in. The lotion may change in color, which is normal and has no impact on its effects.
4, Keep away from clothes to prevent contamination.

Keep out of reach of children. If the product is swallowed, get medical help or contact a Poison Control Center right away.

Package label - Principal display panel

Package Label_Lotion.jpg.

Container Label_Lontion.jpg

Inactive ingredient

Water content: 199980 mg/package